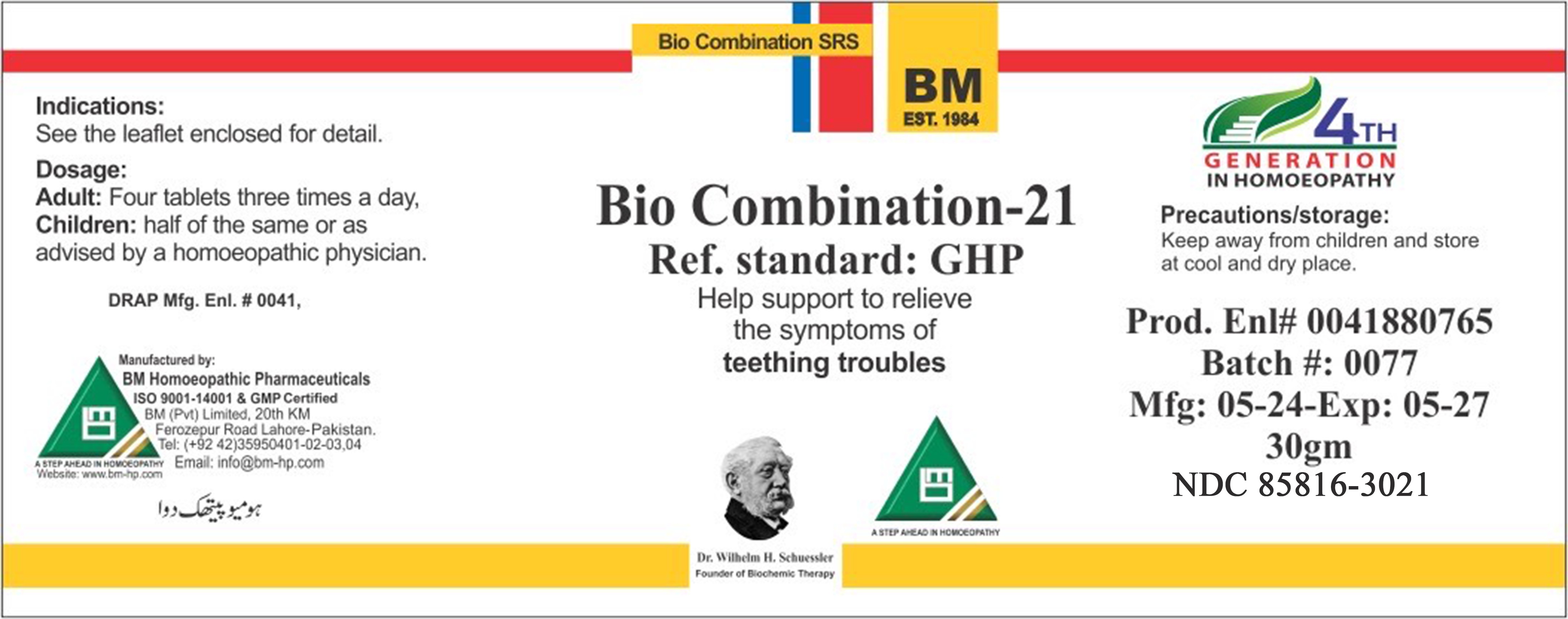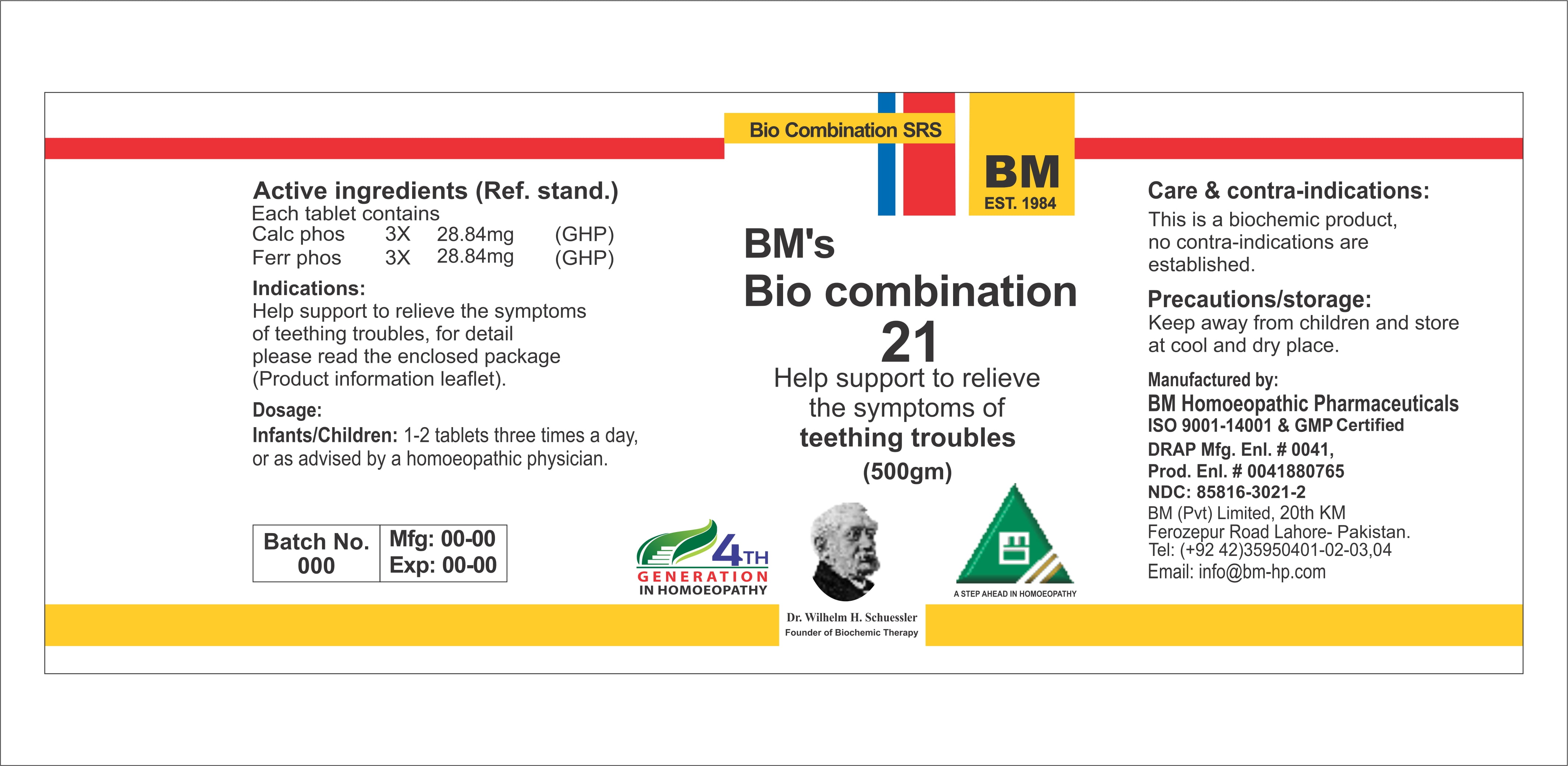 DRUG LABEL: BIO COM 21
NDC: 85816-3021 | Form: GLOBULE
Manufacturer: BM Private Limited
Category: homeopathic | Type: HUMAN OTC DRUG LABEL
Date: 20260217

ACTIVE INGREDIENTS: TRIBASIC CALCIUM PHOSPHATE 6 [hp_X]/1 g; FERROSOFERRIC PHOSPHATE 6 [hp_X]/1 g
INACTIVE INGREDIENTS: MAGNESIUM STEARATE 0.0208 g/1 g; LACTOSE, UNSPECIFIED FORM 0.978 g/1 g

BM HOMEOPATHIC REMEDY BIO COM 21 TEETHING TROUBLES/ BIO21

Dosage:
Adults: Four tablets three times a day.
Children: half of the same or as advised by a homeopathic physician.

ACTIVE INGREDIENT

Calc phos
Ferr phos

INACTIVE INGREDIENT

LACTOSE, MAGNESIUM STEARATE

INDICATIONS AND USAGE

See the enclosed detail for detail

PURPOSE

See the enclosed detail for detail

KEEP OUT OF REACH OF CHILDREN

Precautions/storage:
Keep away from children and store at cool and dry place.

WARNINGS

Precautions/storage:
Keep away from children and store at cool and dry place.

Package 1

Package 2